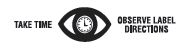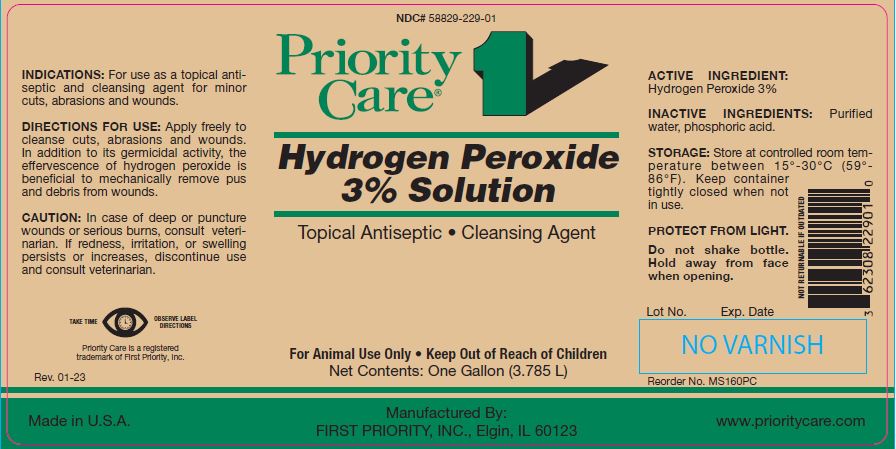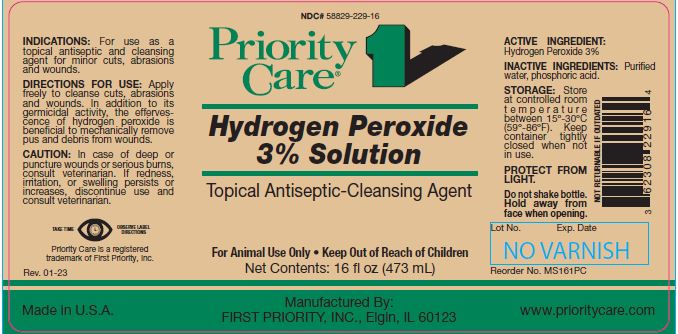 DRUG LABEL: Hydrogen Peroxide
NDC: 58829-229 | Form: SOLUTION
Manufacturer: FIRST PRIORITY INCORPORATED
Category: animal | Type: OTC ANIMAL DRUG LABEL
Date: 20240806

ACTIVE INGREDIENTS: HYDROGEN PEROXIDE 59.2 g/1 L

Hydrogen Peroxide 3% Solution

PURPOSE

Topical Antiseptic-Cleansing Agent

KEEP OUT OF REACH OF CHILDREN

For Animal Use Only • Keep Out of Reach of Children

INDICATIONS:

For use as a topical antiseptic and cleansing agent for minor cuts, abrasions and wounds.

DIRECTIONS FOR USE:

Apply freely to cleanse cuts, abrasions and wounds. In addition to its germicidal activity, the effervescence of hydrogen peroxide is beneficial to mechanically remove pus and debris from wounds.

CAUTION:

In case of deep or puncture wounds or serious burns, consult veterinarian. If redness, irritation, or swelling persists or increases, discontinue use and consult veterinarian.

ACTIVE INGREDIENT:

Hydrogen Peroxide 3%

INACTIVE INGREDIENTS:

Purified water, phosphoric acid.

STORAGE:

Store at controlled room temperature between 15º to 30ºC (59º-86ºF). Keep container tightly closed when not in use.

PROTECT FROM LIGHT.

Do not shake bottle. Hold away from face when opening.

Net Contents:

16 fl oz (473 mL) Reorder No. MS161PC

One Gallon (3.785 L) Reorder No. MS160PC

INFORMATION FOR OWNERS/CAREGIVERS

Priority Care is a registered trademark of First Priority, Inc.

Made in U.S.A. Manufactured By: FIRST PRIORITY, INC., Elgin, IL 60123 www.prioritycare.com

NOT RETURNABLE IF OUTDATED